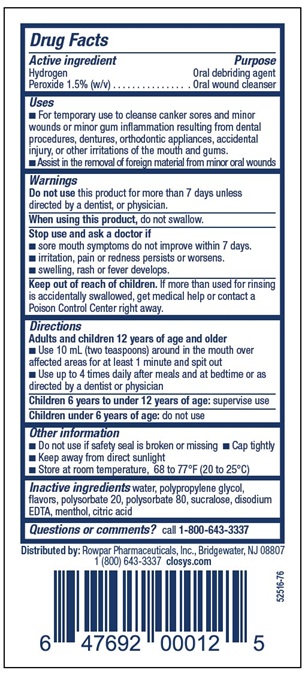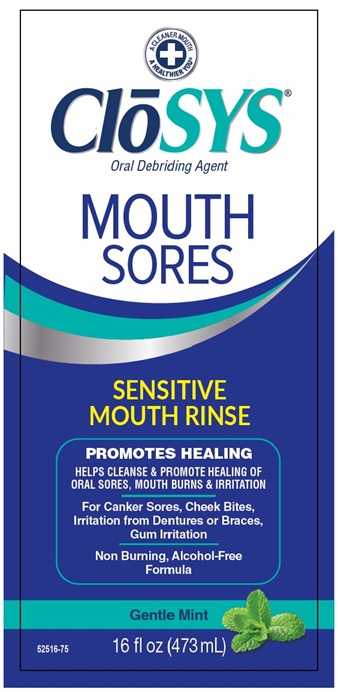 DRUG LABEL: CloSYS
NDC: 58578-0613 | Form: RINSE
Manufacturer: Rowpar Pharmaceuticals, Inc.
Category: otc | Type: HUMAN OTC DRUG LABEL
Date: 20251217

ACTIVE INGREDIENTS: Hydrogen Peroxide 1.5 g/100 mL
INACTIVE INGREDIENTS: Water; Propylene Glycol; Polysorbate 20; Polysorbate 80; Sucralose; Edetate Disodium; Menthol, Unspecified Form; Citric Acid Monohydrate

CloSYS Mouth Sores Oral Rinse

Active ingredient

Hydrogen Peroxide 1.5% (w/v)

Purpose

Oral debriding agent
Oral wound cleanser

Uses

- For temporary use to cleanse canker sores and minor wounds or minor gum inflammation resulting from dental procedures, dentures, orthodontic appliances, accidental injury, or other irritations of the mouth and gums.
- Assist in the removal of foreign material from minor oral wounds.

Do not use this product for more than 7 days unless directed by a dentist, or physician.

When using this product, do not swallow.

Stop use and ask a doctor if

- sore mouth symptoms do not improve within 7 days.
- irritation, pain or redness persists or worsens.
- swelling, rash or fever develops.

Keep out of reach of children. If more than used for rinsing is accidentally swallowed, get medical help or contact a Poison Control Center right away.

Directions

Adults and children 12 years of age and older

- Use 10 mL (two teaspoons) around in the mouth over affected areas for at least 1 minute and spit out
- Use up to 4 times daily after meals and at bedtime or as directed by a dentist or physician

Children 6 years to under 12 years of age: supervise use

Children under 6 years of age: do not use

Other Information

- Do not use if safety seal is broken or missing
- Cap tightly
- Keep away from direct sunlight
- Store at room temperature, 68 to 77°F (20 to 25°C)

Inactive ingredients

water, polypropylene glycol, flavors, polysorbate 20, polysorbate 80, sucralose, disodium EDTA, menthol, citric acid

Questions or comments?

call 1-800-643-3337

Packaging

A CLEANER MOUTH
A HEALTHIER YOU®
CLoSYS®
Oral Debriding Agent
MOUTH
SORES
SENSITIVE
MOUTH RINSE
PROMOTES HEALING
HELPS CLEANSE & PROMOTE HEALING OF
ORAL SORES, MOUTH BURNS & IRRITATION
For Canker Sores, Cheek Bites,
Irritation from Dentures or Braces,
Gum Irritation
Non Burning, Alcohol-Free
Formula
Gentle Mint
16 fl oz (473mL)
52516-75

Distributed by: Rowpar Pharmaceuticals, Inc., Bridgewater, NJ 08807
1 (800) 643-3337 closys.com
52516-76